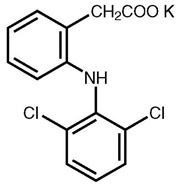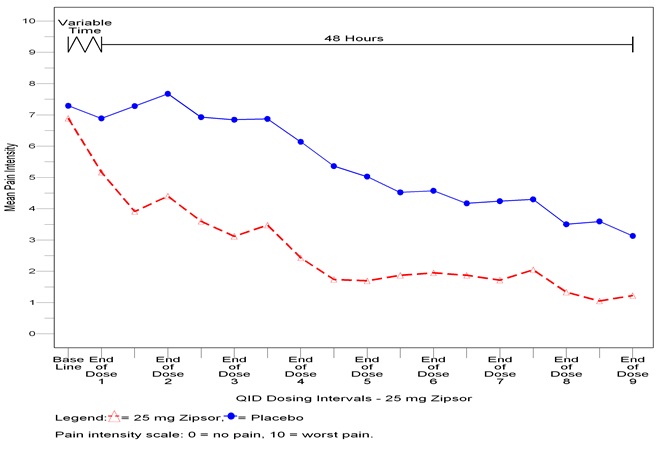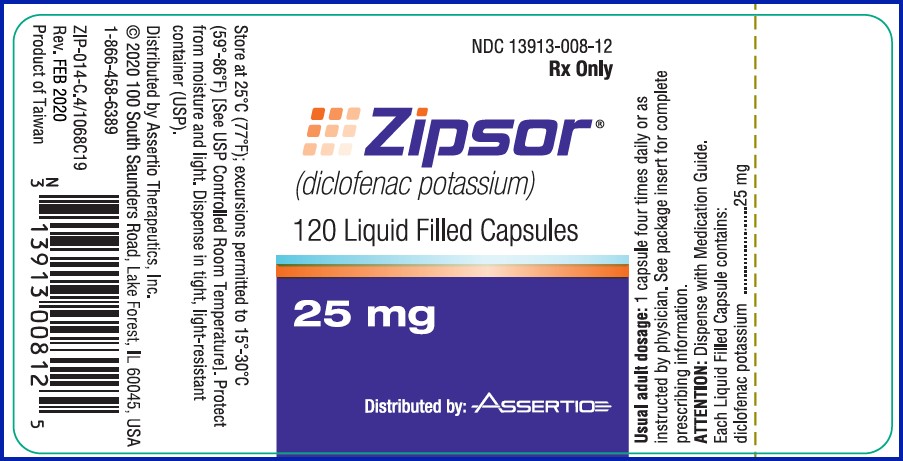 DRUG LABEL: ZIPSOR
NDC: 13913-008 | Form: CAPSULE, LIQUID FILLED
Manufacturer: Assertio Therapeutics, Inc.
Category: prescription | Type: HUMAN PRESCRIPTION DRUG LABEL
Date: 20250903

ACTIVE INGREDIENTS: DICLOFENAC POTASSIUM 25 mg/1 1
INACTIVE INGREDIENTS: POLYETHYLENE GLYCOL 400; GLYCERIN; SORBITOL; POVIDONE; POLYSORBATE 80; HYDROCHLORIC ACID; ISOPROPYL ALCOHOL; MINERAL OIL; GELATIN

HIGHLIGHTS OF PRESCRIBING INFORMATION

These highlights do not include all the information needed to use ZIPSOR® safely and effectively. See full prescribing information for ZIPSOR.
ZIPSOR® (diclofenac potassium) 25 mg capsule, for oral use
Initial U.S. Approval: 1988

WARNING: RISK OF SERIOUS CARDIOVASCULAR AND GASTROINTESTINAL EVENTS

See full prescribing information for complete boxed warning.

- Nonsteroidal anti-inflammatory drugs (NSAIDs) cause an increased risk of serious cardiovascular thrombotic events, including myocardial infarction and stroke, which can be fatal. This risk may occur early in treatment and may increase with duration of use (5.1)
- ZIPSOR is contraindicated in the setting of coronary artery bypass graft (CABG) surgery (4, 5.1)
- NSAIDs cause an increased risk of serious gastrointestinal (GI) adverse events including bleeding, ulceration, and perforation of the stomach or intestines, which can be fatal. These events can occur at any time during use and without warning symptoms. Elderly patients and patients with a prior history of peptic ulcer disease and/or GI bleeding are at greater risk for serious GI events (5.2)

RECENT MAJOR CHANGES

Warnings and Precautions (5.9) | 11/2024

1 INDICATIONS AND USAGE

ZIPSOR is a non-steroidal anti-inflammatory drug indicated for relief of mild to moderate acute pain in adult and pediatric patients 12 years of age and older. (1)

2 DOSAGE AND ADMINISTRATION

- Use the lowest effective dosage for shortest duration consistent with individual patient treatment goals (2.1)
- The dosage is 25 mg four times a day

3 DOSAGE FORMS AND STRENGTHS

ZIPSOR (diclofenac potassium) capsule: 25 mg (3)

4 CONTRAINDICATIONS

- Known hypersensitivity to diclofenac or any components of the drug product (4)
- History of asthma, urticaria, or other allergic-type reactions after taking aspirin or other NSAIDs (4)
- In the setting of CABG surgery (4)
- ZIPSOR contains gelatin and should not be given to patients with known hypersensitivity to bovine protein. (4)

5 WARNINGS AND PRECAUTIONS

- Hepatotoxicity: Inform patients of warning signs and symptoms of hepatotoxicity. Discontinue if abnormal liver tests persist or worsen or if clinical signs and symptoms of liver disease develop (5.3)
- Hypertension: Patients taking some antihypertensive medications may have impaired response to these therapies when taking NSAIDs. Monitor blood pressure (5.4,7)
- Heart Failure and Edema: Avoid use of ZIPSOR in patients with severe heart failure unless benefits are expected to outweigh risk of worsening heart failure (5.5)
- Renal Toxicity: Monitor renal function in patients with renal or hepatic impairment, heart failure, dehydration, or hypovolemia. Avoid use of ZIPSOR in patients with advanced renal disease unless benefits are expected to outweigh risk of worsening renal function (5.6)
- Anaphylactic Reactions: Seek emergency help if an anaphylactic reaction occurs (5.7)
- Exacerbation of Asthma Related to Aspirin Sensitivity: ZIPSOR is contraindicated in patients with aspirin-sensitive asthma. Monitor patients with preexisting asthma (without aspirin sensitivity) (5.8)
- Serious Skin Reactions: Discontinue ZIPSOR at first appearance of skin rash or other signs of hypersensitivity (5.9)
- Drug Reaction with Eosinophilia and Systemic Symptoms (DRESS): Discontinue and evaluate clinically (5.10).
- Fetal Toxicity: Limit use of NSAIDs, including ZIPSOR, between about 20 to 30 weeks in pregnancy due to the risk of oligohydramnios/fetal renal dysfunction. Avoid use of NSAIDs in women at about 30 weeks gestation and later in pregnancy due to the risks of oligohydramnios/fetal renal dysfunction and premature closure of the fetal ductus arteriosus (5.11, 8.1).
- Hematologic Toxicity: Monitor hemoglobin or hematocrit in patients with any signs or symptoms of anemia (5.12, 7)

6 ADVERSE REACTIONS

Most common adverse reactions (incidence ≥ 1%) are gastrointestinal experiences including abdominal pain, constipation, diarrhea, dyspepsia, nausea, vomiting, dizziness, headache, somnolence, pruritus, and increased sweating (6.1)
To report SUSPECTED ADVERSE REACTIONS, contact Assertio Therapeutics, Inc. at 1-866-458-6389 or FDA at 1-800-FDA-1088 or www.fda.gov/medwatch.

7 DRUG INTERACTIONS

- Drugs that Interfere with Hemostasis (e.g. warfarin, aspirin, SSRIs/SNRIs): Monitor patients for bleeding who are concomitantly taking ZIPSOR with drugs that interfere with hemostasis. Concomitant use of ZIPSOR and analgesic doses of aspirin is not generally recommended (7)
- ACE Inhibitors, Angiotensin Receptor Blockers (ARB), or Beta-Blockers: Concomitant use with ZIPSOR may diminish the antihypertensive effect of these drugs. Monitor blood pressure (7)
- ACE Inhibitors and ARBs: Concomitant use with ZIPSOR in elderly, volume depleted, or those with renal impairment may result in deterioration of renal function. In such high risk patients, monitor for signs of worsening renal function (7)
- Diuretics: NSAIDs can reduce natriuretic effect of furosemide and thiazide diuretics. Monitor patients to assure diuretic efficacy including antihypertensive effects (7)
- Digoxin: Concomitant use with ZIPSOR can increase serum concentration and prolong half-life of digoxin. Monitor serum digoxin levels (7)

8 USE IN SPECIFIC POPULATIONS

Infertility: NSAIDs are associated with reversible infertility. Consider withdrawal of ZIPSOR in women who have difficulties conceiving (8.3)

FULL PRESCRIBING INFORMATION

WARNING: RISK OF SERIOUS CARDIOVASCULAR AND GASTROINTESTINAL EVENTS

Cardiovascular Thrombotic Events

- Nonsteroidal anti-inflammatory drugs (NSAIDs) cause an increased risk of serious cardiovascular thrombotic events, including myocardial infarction and stroke, which can be fatal. This risk may occur early in treatment and may increase with duration of use [see Warnings and Precautions (5.1)].
- ZIPSOR is contraindicated in the setting of coronary artery bypass graft (CABG) surgery [see Contraindications (4) and Warnings and Precautions (5.1)].

Gastrointestinal Bleeding, Ulceration, and Perforation

- NSAIDs cause an increased risk of serious gastrointestinal (GI) adverse events including bleeding, ulceration, and perforation of the stomach or intestines, which can be fatal. These events can occur at any time during use and without warning symptoms. Elderly patients and patients with a prior history of peptic ulcer disease and/or GI bleeding are at greater risk for serious GI events [see Warnings and Precautions (5.2)].

1 INDICATIONS AND USAGE

ZIPSOR is indicated for relief of mild to moderate acute pain in adult and pediatric patients 12 years of age and older.

2 DOSAGE AND ADMINISTRATION

2.1 General Dosing Instructions

Carefully consider the potential benefits and risks of ZIPSOR and other treatment options before deciding to use ZIPSOR. Use the lowest effective dosage for the shortest duration consistent with individual patient treatment goals [see Warnings and Precautions (5)].

For treatment of mild to moderate acute pain in adult and pediatric patients 12 years of age and older, the dosage is 25 mg four times a day.

2.2 Dosage Adjustments in Patients with Hepatic Impairment

Patients with hepatic disease may require reduced doses of ZIPSOR compared to patients with normal hepatic function [see Clinical Pharmacology (12)]. As with other diclofenac products, start treatment at the lowest dose. If efficacy is not achieved with the lowest dose, discontinue use.

2.3 Non-Interchangeability with Other Formulations of Diclofenac

Different dose strengths and formulations of oral diclofenac are not interchangeable. This difference should be taken into consideration when changing strengths or formulations. The only approved dosing regimen for ZIPSOR is 25 mg four times a day.

3 DOSAGE FORMS AND STRENGTHS

ZIPSOR (diclofenac potassium) capsule: 25 mg

4 CONTRAINDICATIONS

ZIPSOR is contraindicated in the following patients:

- Known hypersensitivity (e.g., anaphylactic reactions and serious skin reactions) to diclofenac or any components of the drug product [see Warnings and Precautions (5.7, 5.9)]
- History of asthma, urticaria, or other allergic-type reactions after taking aspirin or other NSAIDs. Severe, sometimes fatal, anaphylactic reactions to NSAIDs have been reported in such patients [see Warnings and Precautions (5.7, 5.8)]
- In the setting of coronary artery bypass graft (CABG) surgery [see Warnings and Precautions (5.1)]
- ZIPSOR contains gelatin and is contraindicated in patients with known hypersensitivity to bovine protein.

5 WARNINGS AND PRECAUTIONS

5.1 Cardiovascular Thrombotic Events

Clinical trials of several COX-2 selective and nonselective NSAIDs of up to three years duration have shown an increased risk of serious cardiovascular (CV) thrombotic events, including myocardial infarction (MI) and stroke, which can be fatal. Based on available data, it is unclear that the risk for CV thrombotic events is similar for all NSAIDs. The relative increase in serious CV thrombotic events over baseline conferred by NSAID use appears to be similar in those with and without known CV disease or risk factors for CV disease. However, patients with known CV disease or risk factors had a higher absolute incidence of excess serious CV thrombotic events, due to their increased baseline rate. Some observational studies found that this increased risk of serious CV thrombotic events began as early as the first weeks of treatment. The increase in CV thrombotic risk has been observed most consistently at higher doses.

To minimize the potential risk for an adverse CV event in NSAID-treated patients, use the lowest effective dose for the shortest duration possible. Physicians and patients should remain alert for the development of such events, throughout the entire treatment course, even in the absence of previous CV symptoms. Patients should be informed about the symptoms of serious CV events and the steps to take if they occur.

There is no consistent evidence that concurrent use of aspirin mitigates the increased risk of serious CV thrombotic events associated with NSAID use. The concurrent use of aspirin and an NSAID, such as diclofenac, increases the risk of serious gastrointestinal (GI) events [see Warnings and Precautions (5.2)].

Status Post Coronary Artery Bypass Graft (CABG) Surgery

Two large, controlled clinical trials of a COX-2 selective NSAID for the treatment of pain in the first 10–14 days following CABG surgery found an increased incidence of myocardial infarction and stroke. NSAIDs are contraindicated in the setting of CABG [see Contraindications (4)].

Post-MI Patients

Observational studies conducted in the Danish National Registry have demonstrated that patients treated with NSAIDs in the post-MI period were at increased risk of reinfarction, CV-related death, and all-cause mortality beginning in the first week of treatment. In this same cohort, the incidence of death in the first year post-MI was 20 per 100 person years in NSAID-treated patients compared to 12 per 100 person years in non-NSAID exposed patients. Although the absolute rate of death declined somewhat after the first year post-MI, the increased relative risk of death in NSAID users persisted over at least the next four years of follow-up.

Avoid the use of ZIPSOR in patients with a recent MI unless the benefits are expected to outweigh the risk of recurrent CV thrombotic events. If ZIPSOR is used in patients with a recent MI, monitor patients for signs of cardiac ischemia.

5.2 Gastrointestinal Bleeding, Ulceration, and Perforation

NSAIDs, including diclofenac, cause serious gastrointestinal (GI) adverse events including inflammation, bleeding, ulceration, and perforation of the esophagus, stomach, small intestine, or large intestine, which can be fatal. These serious adverse events can occur at any time, with or without warning symptoms, in patients treated with NSAIDs. Only one in five patients who develop a serious upper GI adverse event on NSAID therapy is symptomatic. Upper GI ulcers, gross bleeding, or perforation caused by NSAIDs occurred in approximately 1% of patients treated for 3-6 months, and in about 2%-4% of patients treated for one year. However, even short-term NSAID therapy is not without risk.

Risk Factors for GI Bleeding, Ulceration, and Perforation

Patients with a prior history of peptic ulcer disease and/or GI bleeding who used NSAIDs had a greater than 10-fold increased risk for developing a GI bleed compared to patients without these risk factors. Other factors that increase the risk of GI bleeding in patients treated with NSAIDs include longer duration of NSAID therapy; concomitant use of oral corticosteroids, aspirin, anticoagulants, or selective serotonin reuptake inhibitors (SSRIs); smoking; use of alcohol; older age; and poor general health status. Most postmarketing reports of fatal GI events occurred in elderly or debilitated patients. Additionally, patients with advanced liver disease and/or coagulopathy are at increased risk for GI bleeding.

Strategies to Minimize the GI Risks in NSAID-treated patients:

- Use the lowest effective dosage for the shortest possible duration.
- Avoid administration of more than one NSAID at a time.
- Avoid use in patients at higher risk unless benefits are expected to outweigh the increased risk of bleeding. For such patients, as well as those with active GI bleeding, consider alternate therapies other than NSAIDs.
- Remain alert for signs and symptoms of GI ulceration and bleeding during NSAID therapy.
- If a serious GI adverse event is suspected, promptly initiate evaluation and treatment, and discontinue ZIPSOR until a serious GI adverse event is ruled out.
- In the setting of concomitant use of low-dose aspirin for cardiac prophylaxis, monitor patients more closely for evidence of GI bleeding [see Drug Interactions (7)].

5.3 Hepatotoxicity

In clinical trials of diclofenac-containing products, meaningful elevations (i.e., more than 3 times the ULN) of AST (SGOT) were observed in about 2% of approximately 5,700 patients at some time during diclofenac treatment (ALT was not measured in all studies).

In a large open-label, controlled trial of 3,700 patients treated with oral diclofenac sodium for 2–6 months, patients were monitored first at 8 weeks and 1,200 patients were monitored again at 24 weeks. Meaningful elevations of ALT and/or AST occurred in about 4% of the 3,700 patients and included marked elevations (greater than 8 times the ULN) in about 1% of the 3,700 patients. In that open-label study, a higher incidence of borderline (less than 3 times the ULN), moderate (3–8 times the ULN), and marked (greater than 8 times the ULN) elevations of ALT or AST was observed in patients receiving diclofenac when compared to other NSAIDs. Elevations in transaminases were seen more frequently in patients with osteoarthritis than in those with rheumatoid arthritis.

Almost all meaningful elevations in transaminases were detected before patients became symptomatic. Abnormal tests occurred during the first 2 months of therapy with diclofenac in 42 of the 51 patients in all trials who developed marked transaminase elevations.

In postmarketing reports, cases of drug-induced hepatotoxicity have been reported in the first month, and in some cases, the first 2 months of NSAID therapy, but can occur at any time during treatment with diclofenac. Postmarketing surveillance has reported cases of severe hepatic reactions, including liver necrosis, jaundice, fulminant hepatitis with and without jaundice, and liver failure. Some of these reported cases resulted in fatalities or liver transplantation.

In a European retrospective population-based, case-controlled study, 10 cases of diclofenac associated drug-induced liver injury with current use compared with non-use of diclofenac were associated with a statistically significant 4-fold adjusted odds ratio of liver injury. In this particular study, based on an overall number of 10 cases of liver injury associated with diclofenac, the adjusted odds ratio increased further with female sex, doses of 150 mg or more, and duration of use for more then 90 days.

Physicians should measure transaminases at baseline and periodically in patients receiving long-term therapy with ZIPSOR, because severe hepatotoxicity may develop without a prodrome of distinguishing symptoms. The optimum times for making the first and subsequent transaminase measurements are not known. Based on clinical trial data and postmarketing experiences, transaminases should be monitored within 4 to 8 weeks after initiating treatment with diclofenac. However, severe hepatic reactions can occur at any time during treatment with diclofenac.

If abnormal liver tests persist or worsen, if clinical signs and/or symptoms consistent with liver disease develop, or if systemic manifestations occur (e.g., eosinophilia, rash, abdominal pain, diarrhea, dark urine, etc.), ZIPSOR should be discontinued immediately.

Inform patients of the warning signs and symptoms of hepatotoxicity (e.g., nausea, fatigue, lethargy, diarrhea, pruritus, jaundice, right upper quadrant tenderness, and "flu-like" symptoms). If clinical signs and symptoms consistent with liver disease develop, or if systemic manifestations occur (e.g., eosinophilia, rash, etc.), discontinue ZIPSOR immediately, and perform a clinical evaluation of the patient.

To minimize the potential risk for an adverse liver-related event in patients treated with ZIPSOR, use the lowest effective dose for the shortest duration possible. Exercise caution when prescribing ZIPSOR with concomitant drugs that are known to be potentially hepatotoxic (e.g., acetaminophen, antibiotics, antiepileptics).

5.4 Hypertension

NSAIDs, including ZIPSOR, can lead to new onset of hypertension or worsening of pre- existing hypertension, either of which may contribute to the increased incidence of CV events. Patients taking angiotensin converting enzyme (ACE) inhibitors, thiazide diuretics, or loop diuretics may have impaired response to these therapies when taking NSAIDs [see Drug Interactions (7)].

Monitor blood pressure (BP) during the initiation of NSAID treatment and throughout the course of therapy.

5.5 Heart Failure and Edema

The Coxib and traditional NSAID Trialists’ Collaboration meta-analysis of randomized controlled trials demonstrated an approximately two-fold increase in hospitalizations for heart failure in COX-2 selective-treated patients and nonselective NSAID-treated patients compared to placebo-treated patients. In a Danish National Registry study of patients with heart failure, NSAID use increased the risk of MI, hospitalization for heart failure, and death.

Additionally, fluid retention and edema have been observed in some patients treated with NSAIDs. Use of diclofenac may blunt the CV effects of several therapeutic agents used to treat these medical conditions (e.g., diuretics, ACE inhibitors, or angiotensin receptor blockers [ARBs]) [see Drug Interactions (7)].

Avoid the use of ZIPSOR in patients with severe heart failure unless the benefits are expected to outweigh the risk of worsening heart failure. If ZIPSOR is used in patients with severe heart failure, monitor patients for signs of worsening heart failure.

5.6 Renal Toxicity and Hyperkalemia

Renal Toxicity
Long-term administration of NSAIDs has resulted in renal papillary necrosis and other renal injury.

Renal toxicity has also been seen in patients in whom renal prostaglandins have a compensatory role in the maintenance of renal perfusion. In these patients, administration of an NSAID may cause a dose-dependent reduction in prostaglandin formation and, secondarily, in renal blood flow, which may precipitate overt renal decompensation. Patients at greatest risk of this reaction are those with impaired renal function, dehydration, hypovolemia, heart failure, liver dysfunction, those taking diuretics and ACE inhibitors or ARBs, and the elderly. Discontinuation of NSAID therapy is usually followed by recovery to the pretreatment state.

No information is available from controlled clinical studies regarding the use of ZIPSOR in patients with advanced renal disease. The renal effects of ZIPSOR may hasten the progression of renal dysfunction in patients with preexisting renal disease.

Correct volume status in dehydrated or hypovolemic patients prior to initiating ZIPSOR. Monitor renal function in patients with renal or hepatic impairment, heart failure, dehydration, or hypovolemia during use of ZIPSOR [see Drug Interactions (7)]. Avoid the use of ZIPSOR in patients with advanced renal disease unless the benefits are expected to outweigh the risk of worsening renal function. If ZIPSOR is used in patients with advanced renal disease, monitor patients for signs of worsening renal function.

Hyperkalemia
Increases in serum potassium concentration, including hyperkalemia, have been reported with use of NSAIDs, even in some patients without renal impairment. In patients with normal renal function, these effects have been attributed to a hyporeninemic-hypoaldosteronism state.

5.7 Anaphylactic Reactions

Diclofenac has been associated with anaphylactic reactions in patients with and without known hypersensitivity to diclofenac and in patients with aspirin-sensitive asthma [see Contraindications (4) and Warnings and Precautions (5.8)].

Seek emergency help if an anaphylactic reaction occurs.

5.8 Exacerbation of Asthma Related to Aspirin Sensitivity

A subpopulation of patients with asthma may have aspirin-sensitive asthma which may include chronic rhinosinusitis complicated by nasal polyps; severe, potentially fatal bronchospasm; and/or intolerance to aspirin and other NSAIDs. Because cross-reactivity between aspirin and other NSAIDs has been reported in such aspirin-sensitive patients, ZIPSOR is contraindicated in patients with this form of aspirin sensitivity [see Contraindications (4)]. When ZIPSOR is used in patients with preexisting asthma (without known aspirin sensitivity), monitor patients for changes in the signs and symptoms of asthma.

5.9 Serious Skin Reactions

NSAIDs, including diclofenac, can cause serious skin adverse reactions such as exfoliative dermatitis, Stevens-Johnson Syndrome (SJS), and toxic epidermal necrolysis (TEN), which can be fatal. NSAIDs can also cause fixed drug eruption (FDE). FDE may present as a more severe variant known as generalized bullous fixed drug eruption (GBFDE), which can be life-threatening. These serious events may occur without warning. Inform patients about the signs and symptoms of serious skin reactions, and to discontinue the use of ZIPSOR at the first appearance of skin rash or any other sign of hypersensitivity. ZIPSOR is contraindicated in patients with previous serious skin reactions to NSAIDs [see Contraindications (4)].

5.10 Drug Reaction with Eosinophilia and Systemic Symptoms (DRESS)

Drug Reaction with Eosinophilia and Systemic Symptoms (DRESS) has been reported in patients taking NSAIDs such as ZIPSOR. Some of these events have been fatal or life-threatening. DRESS typically, although not exclusively, presents with fever, rash, lymphadenopathy, and/or facial swelling. Other clinical manifestations may include hepatitis, nephritis, hematological abnormalities, myocarditis, or myositis. Sometimes symptoms of DRESS may resemble an acute viral infection. Eosinophilia is often present. Because this disorder is variable in its presentation, other organ systems not noted here may be involved. It is important to note that early manifestations of hypersensitivity, such as fever or lymphadenopathy, may be present even though rash is not evident. If such signs or symptoms are present, discontinue ZIPSOR and evaluate the patient immediately.

5.11 Fetal Toxicity

Premature Closure of Fetal Ductus Arteriosus

Avoid use of NSAIDs, including ZIPSOR, in pregnant women at about 30 weeks gestation and later. NSAIDs, including ZIPSOR, increase the risk of premature closure of the fetal ductus arteriosus at approximately this gestational age.

Oligohydramnios/Neonatal Renal Impairment

Use of NSAIDs, including ZIPSOR, at about 20 weeks gestation or later in pregnancy may cause fetal renal dysfunction leading to oligohydramnios and, in some cases, neonatal renal impairment. These adverse outcomes are seen, on average, after days to weeks of treatment, although oligohydramnios has been infrequently reported as soon as 48 hours after NSAID initiation. Oligohydramnios is often, but not always, reversible with treatment discontinuation. Complications of prolonged oligohydramnios may, for example, include limb contractures and delayed lung maturation. In some postmarketing cases of impaired neonatal renal function, invasive procedures such as exchange transfusion or dialysis were required.

If NSAID treatment is necessary between about 20 weeks and 30 weeks gestation, limit ZIPSOR use to the lowest effective dose and shortest duration possible. Consider ultrasound monitoring of amniotic fluid if ZIPSOR treatment extends beyond 48 hours. Discontinue ZIPSOR if oligohydramnios occurs and follow up according to clinical practice [see Use in Specific Populations (8.1)].

5.12 Hematologic Toxicity

Anemia has occurred in NSAID-treated patients. This may be due to occult or gross blood loss, fluid retention, or an incompletely described effect on erythropoiesis. If a patient treated with ZIPSOR has any signs or symptoms of anemia, monitor hemoglobin or hematocrit.

NSAIDs, including ZIPSOR, may increase the risk of bleeding events. Co-morbid conditions such as coagulation disorders or concomitant use of warfarin, other anticoagulants, antiplateletagents (e.g., aspirin), serotonin reuptake inhibitors (SSRIs) and serotonin norepinephrine reuptake inhibitors (SNRIs) may increase this risk. Monitor these patients for signs of bleeding [see Drug Interactions (7)].

5.13 Masking of Inflammation and Fever

The pharmacological activity of ZIPSOR in reducing inflammation, and possibly fever, may diminish the utility of diagnostic signs in detecting infections.

5.14 Laboratory Monitoring

Because serious GI bleeding, hepatotoxicity, and renal injury can occur without warning symptoms or signs, consider monitoring patients on long-term NSAID treatment with a CBC and a chemistry profile periodically [see Warnings and Precautions (5.2, 5.3, 5.6)].

6 ADVERSE REACTIONS

The following adverse reactions are discussed in greater detail in other sections of the labeling:

- Cardiovascular Thrombotic Events [see Warnings and Precautions (5.1)]
- GI Bleeding, Ulceration and Perforation [see Warnings and Precautions (5.2)]
- Hepatotoxicity [see Warnings and Precautions (5.3)]
- Hypertension [see Warnings and Precautions (5.4)]
- Heart Failure and Edema [see Warnings and Precautions (5.5)]
- Renal Toxicity and Hyperkalemia [see Warnings and Precautions (5.6)]
- Anaphylactic Reactions [see Warnings and Precautions (5.7)]
- Serious Skin Reactions [see Warnings and Precautions (5.9)]
- Hematologic Toxicity [see Warnings and Precautions (5.12)]

6.1 Clinical Trials Experience

Because clinical trials are conducted under widely varying conditions, adverse reaction rates observed in clinical trials of a drug cannot be directly compared with the rates in clinical trials of another drug and may not reflect the rates observed in practice.

The safety of ZIPSOR was evaluated in 965 adult subjects. In patients treated with ZIPSOR 25 mg (N=345) or a higher dose, three or four times a day, for 4 to 5 days, the most common adverse reactions (i.e., reported in ≥ 1% of ZIPSOR treated patients) were as follows: gastrointestinal experiences including abdominal pain, constipation, diarrhea, dyspepsia, nausea, vomiting, dizziness, headache, somnolence, pruritus, and increased sweating. (see Table 1).

The safety of ZIPSOR was evaluated in 125 pediatric patients, 12 years to 17 years of age. Forty-nine (49) patients with mild to moderate acute pain from a surgical procedure or an acute painful condition were treated with ZIPSOR 25 mg up to four times a day, for 4 days. Seventy-six (76) pediatric patients who underwent insertion of either orthodontic separators or arch wires were treated with a single-dose of either ZIPSOR 25 mg or ZIPSOR 50 mg after completion of the procedure. The most common adverse reactions in the multiple-dose studies were nausea (14.3%), headache (10.2%), constipation (8.2%), abdominal pain (4.1%), vomiting (4.1%), dizziness (4.1%), back pain (4.1%), and musculoskeletal pain (4.1%).

Table 1 Incidence of Treatment Emergent Adverse Reactions with Incidence ≥ 1% of ZIPSOR Treated Patients in Multiple-Dose Studies
MedDRA System Organ Class and Preferred Term |  | ZIPSOR* 25 mg n=345 n (%) |  | Placebo* n=327 n (%)
Any Adverse Events |  | 144 (41.7) |  | 181 (55.4)
Nausea |  | 57 (16.5) |  | 66 (20.2)
Headache |  | 43 (12.5) |  | 56 (17.1)
Abdominal Pain |  | 24 (7.0) |  | 11 (3.4)
Vomiting |  | 20 (5.8) |  | 17 (5.2)
Dizziness |  | 12 (3.5) |  | 66 (20.2)
Constipation |  | 11 (3.2) |  | 9 (2.8)
Somnolence |  | 9 (2.6) |  | 6 (1.8)
Diarrhea |  | 8 (2.3) |  | 9 (2.8)
Pruritus |  | 5 (1.4) |  | 6 (1.8)
Dyspepsia |  | 4 (1.2) |  | 8 (2.4)
Sweating Increase |  | 4 (1.2) |  | 2 (0.6)
*There was greater use of concomitant opioid rescue medication in placebo treated patients than in ZIPSOR treated patients

In patients taking other NSAIDs, the most frequently reported adverse experiences occurring in approximately 1%-10% of patients are:

Gastrointestinal experiences including: abdominal pain, constipation, diarrhea, dyspepsia, flatulence, gross bleeding/perforation, heartburn, nausea, GI ulcers (gastric/duodenal) and vomiting.

Abnormal renal function, anemia, dizziness, edema, elevated liver enzymes, headaches, increased bleeding time, pruritus, rashes, and tinnitus.

Additional adverse experiences reported in patients taking other NSAIDs occasionally include:

Body as a Whole: fever, infection, sepsis
Cardiovascular System: congestive heart failure, hypertension, tachycardia, syncope
Digestive System: dry mouth, esophagitis, gastric/peptic ulcers, gastritis, gastrointestinal bleeding, glossitis, hematemesis, hepatitis, jaundice
Hemic and Lymphatic System: ecchymosis, eosinophilia, leukopenia, melena, purpura, rectal bleeding, stomatitis, thrombocytopenia
Metabolic and Nutritional: weight changes
Nervous System: anxiety, asthenia, confusion, depression, dream abnormalities, drowsiness, insomnia, malaise, nervousness, paresthesia, somnolence, tremors, vertigo
Respiratory System: asthma, dyspnea
Skin and Appendages: alopecia, photosensitivity, sweating increased
Special Senses: blurred vision
Urogenital System: cystitis, dysuria, hematuria, interstitial nephritis, oliguria/polyuria, proteinuria, renal failure

Other adverse reactions in patients taking other NSAIDs, which occur rarely are:
Body as a Whole: anaphylactic reactions, appetite changes, death
Cardiovascular System: arrhythmia, hypotension, myocardial infarction, palpitations, vasculitis
Digestive System: colitis, eructation, liver failure, pancreatitis
Hemic and Lymphatic System: agranulocytosis, hemolytic anemia, aplastic anemia, lymphadenopathy, pancytopenia
Metabolic and Nutritional: hyperglycemia
Nervous System: convulsions, coma, hallucinations, meningitis
Respiratory System: respiratory depression, pneumonia
Skin and Appendages: angioedema, toxic epidermal necrolysis, erythema multiforme, exfoliative dermatitis, Stevens-Johnson Syndrome, urticaria
Special Senses: conjunctivitis, hearing impairment

6.2 Postmarketing Experience

The following adverse reactions have been identified during postapproval use of diclofenac. Because these reactions are reported voluntarily from a population of uncertain size, it is not always possible to reliably estimate their frequency or establish a causal relationship to drug exposure.

Skin and Appendages: Exfoliative dermatitis, Stevens-Johnson Syndrome (SJS), toxic epidermal necrolysis (TEN), and fixed drug eruption (FDE).

7 DRUG INTERACTIONS

See Table 2 for clinically significant drug interactions with diclofenac.

Table 2: Clinically Significant Drug Interactions with diclofenac
Drugs That Interfere with Hemostasis
Clinical Impact: | - Diclofenac and anticoagulants such as warfarin have a synergistic effect on bleeding. The concomitant use of diclofenac and anticoagulants have an increased risk of serious bleeding compared to the use of either drug alone. - Serotonin release by platelets plays an important role in hemostasis. Case-control and cohort epidemiological studies showed that concomitant use of drugs that interfere with serotonin reuptake and an NSAID may potentiate the risk of bleeding more than an NSAID alone.
Intervention: | Monitor patients with concomitant use of ZIPSOR with anticoagulants (e.g., warfarin), antiplatelet agents (e.g., aspirin), selective serotonin reuptake inhibitors (SSRIs), and serotonin norepinephrine reuptake inhibitors (SNRIs) for signs of bleeding [see Warnings and Precautions (5.12)].
Aspirin
Clinical Impact: | Controlled clinical studies showed that the concomitant use of NSAIDs and analgesic doses of aspirin does not produce any greater therapeutic effect than the use of NSAIDs alone. In a clinical study, the concomitant use of an NSAID and aspirin was associated with a significantly increased incidence of GI adverse reactions as compared to use of the NSAID alone [see Warnings and Precautions (5.2)].
Intervention: | Concomitant use of ZIPSOR and analgesic doses of aspirin is not generally recommended because of the increased risk of bleeding [see Warnings and Precautions (5.12)]. ZIPSOR is not a substitute for low dose aspirin for cardiovascular protection.
ACE Inhibitors, Angiotensin Receptor Blockers, and Beta-Blockers
Clinical Impact: | - NSAIDs may diminish the antihypertensive effect of angiotensin converting enzyme (ACE) inhibitors, angiotensin receptor blockers (ARBs), or beta-blockers (including propranolol). - In patients who are elderly, volume-depleted (including those on diuretic therapy), or have renal impairment, co-administration of an NSAID with ACE inhibitors or ARBs may result in deterioration of renal function, including possible acute renal failure. These effects are usually reversible.
Intervention: | - During concomitant use of ZIPSOR and ACE-inhibitors, ARBs, or beta-blockers, monitor blood pressure to ensure that the desired blood pressure is obtained. - During concomitant use of ZIPSOR and ACE-inhibitors or ARBs in patients who are elderly, volume-depleted, or have impaired renal function, monitor for signs of worsening renal function [see Warnings and Precautions (5.6)]. - When these drugs are administered concomitantly, patients should be adequately hydrated. Assess renal function at the beginning of the concomitant treatment and periodically thereafter.
Diuretics
Clinical Impact: | Clinical studies, as well as post-marketing observations, showed that NSAIDs reduced the natriuretic effect of loop diuretics (e.g., furosemide) and thiazide diuretics in some patients. This effect has been attributed to the NSAID inhibition of renal prostaglandin synthesis.
Intervention: | During concomitant use of ZIPSOR with diuretics, observe patients for signs of worsening renal function, in addition to assuring diuretic efficacy including antihypertensive effects [see Warnings and Precautions (5.6)].
Digoxin
Clinical Impact: | The concomitant use of diclofenac with digoxin has been reported to increase the serum concentration and prolong the half-life of digoxin.
Intervention: | During concomitant use of ZIPSOR and digoxin, monitor serum digoxin levels.
Lithium
Clinical Impact: | NSAIDs have produced elevations in plasma lithium levels and reductions in renal lithium clearance. The mean minimum lithium concentration increased 15%, and the renal clearance decreased by approximately 20%. This effect has been attributed to NSAID inhibition of renal prostaglandin synthesis.
Intervention: | During concomitant use of ZIPSOR and lithium, monitor patients for signs of lithium toxicity.
Methotrexate
Clinical Impact: | Concomitant use of NSAIDs and methotrexate may increase the risk for methotrexate toxicity (e.g., neutropenia, thrombocytopenia, renal dysfunction).
Intervention: | During concomitant use of ZIPSOR and methotrexate, monitor patients for methotrexate toxicity.
Cyclosporine
Clinical Impact: | Concomitant use of ZIPSOR and cyclosporine may increase cyclosporine’s nephrotoxicity.
Intervention: | During concomitant use of ZIPSOR and cyclosporine, monitor patients for signs of worsening renal function.
NSAIDs and Salicylates
Clinical Impact: | Concomitant use of diclofenac with other NSAIDs or salicylates (e.g., diflunisal, salsalate) increases the risk of GI toxicity, with little or no increase in efficacy [see Warnings and Precautions (5.2)].
Intervention: | The concomitant use of diclofenac with other NSAIDs or salicylates is not recommended.
Pemetrexed
Clinical Impact: | Concomitant use of ZIPSOR and pemetrexed may increase the risk of pemetrexed- associated myelosuppression, renal, and GI toxicity (see the pemetrexed prescribing information).
Intervention: | During concomitant use of ZIPSOR and pemetrexed, in patients with renal impairment whose creatinine clearance ranges from 45 to 79 mL/min, monitor for myelosuppression, renal and GI toxicity. NSAIDs with short elimination half-lives (e.g., diclofenac, indomethacin) should be avoided for a period of two days before, the day of, and two days following administration of pemetrexed. In the absence of data regarding potential interaction between pemetrexed and NSAIDs with longer half-lives (e.g., meloxicam, nabumetone), patients taking these NSAIDs should interrupt dosing for at least five days before, the day of, and two days following pemetrexed administration.
CYP2C9 Inhibitors or Inducers:
Clinical Impact | Diclofenac is metabolized by cytochrome P450 enzymes, predominantly by CYP2C9. Co-administration of diclofenac with CYP2C9 inhibitors (e.g. voriconazole) may enhance the exposure and toxicity of diclofenac whereas co- administration with CYP2C9 inducers (e.g. rifampin) may lead to compromised efficacy of diclofenac.
Intervention: | A dosage adjustment may be warranted when diclofenac is administered with CYP2C9 inhibitors or inducers [see Clinical Pharmacology (12.3)]

8 USE IN SPECIFIC POPULATIONS

8.1 Pregnancy

Risk Summary
Use of NSAIDs, including ZIPSOR, can cause premature closure of the fetal ductus arteriosus and fetal renal dysfunction leading to oligohydramnios and, in some cases, neonatal renal impairment. Because of these risks, limit dose and duration of ZIPSOR use between about 20 and 30 weeks of gestation, and avoid ZIPSOR use at about 30 weeks of gestation and later in pregnancy (see Clinical Considerations, Data).

Premature Closure of Fetal Ductus Arteriosus

Use of NSAIDs, including ZIPSOR, at about 30 weeks gestation or later in pregnancy increases the
risk of premature closure of the fetal ductus arteriosus.

Oligohydramnios/Neonatal Renal Impairment

Use of NSAIDs at about 20 weeks gestation or later in pregnancy has been associated with cases of
fetal renal dysfunction leading to oligohydramnios, and in some cases, neonatal renal impairment.

Data from observational studies regarding other potential embryofetal risks of NSAID use in women in the first or second trimesters of pregnancy are inconclusive.

In animal reproduction studies, no evidence of malformations was observed in mice, rats, and rabbits given diclofenac during the period of organogenesis at doses up to approximately 1, 1, and 2 times, respectively, the maximum recommended human dose (MRHD) of ZIPSOR, despite the presence of maternal and fetal toxicity at these doses. In published studies, administration of clinically relevant doses of diclofenac to pregnant rats produced adverse effects on brain, kidney, and testicular development [see Data]. Based on animal data, prostaglandins have been shown to have an important role in endometrial vascular permeability, blastocyst implantation, and decidualization. In animal studies, administration of prostaglandin synthesis inhibitors such as diclofenac, resulted in increased pre- and post-implantation loss. Prostaglandins also have been shown to have an important role in fetal kidney development. In published animal studies, prostaglandin synthesis inhibitors have been reported to impair kidney development when administered at clinically relevant doses.

The estimated background risk of major birth defects and miscarriage for the indicated population(s) is unknown. All pregnancies have a background risk of birth defect, loss, or other adverse outcomes. In the U.S. general population, the estimated background risk of major birth defects and miscarriage in clinically recognized pregnancies is 2 to 4% and 15 to 20%, respectively.

Clinical Considerations

Fetal/Neonatal Adverse Reactions

Premature Closure of Fetal Ductus Arteriosus:

Avoid use of NSAIDs in women at about 30 weeks gestation and later in pregnancy, because NSAIDs, including ZIPSOR, can cause premature closure of the fetal ductus arteriosus (see Data).

Oligohydramnios/Neonatal Renal Impairment:

If an NSAID is necessary at about 20 weeks gestation or later in pregnancy, limit the use to the lowest dose and shortest duration possible. If ZIPSOR treatment extends beyond 48 hours, consider monitoring with ultrasound for oligohydramnios. If oligohydramnios occurs, discontinue ZIPSOR and follow up according to clinical practice (see Data).

Labor or Delivery
There are no studies on the effects of ZIPSOR during labor or delivery. In animal studies, NSAIDS, including diclofenac, inhibit prostaglandin synthesis, cause delayed parturition, and increase the incidence of stillbirth.

Data

Human Data

Premature Closure of Fetal Ductus Arteriosus:

Published literature reports that the use of NSAIDs at about 30 weeks of gestation and later in pregnancy may cause premature closure of the fetal ductus arteriosus.

Oligohydramnios/Neonatal Renal Impairment:

Published studies and postmarketing reports describe maternal NSAID use at about 20 weeks gestation or later in pregnancy associated with fetal renal dysfunction leading to oligohydramnios, and in some cases, neonatal renal impairment. These adverse outcomes are seen, on average, after days to weeks of treatment, although oligohydramnios has been infrequently reported as soon as 48 hours after NSAID initiation. In many cases, but not all, the decrease in amniotic fluid was transient and reversible with cessation of the drug. There have been a limited number of case reports of maternal NSAID use and neonatal renal dysfunction without oligohydramnios, some of which were irreversible. Some cases of neonatal renal dysfunction required treatment with invasive procedures, such as exchange transfusion or dialysis.

Methodological limitations of these postmarketing studies and reports include lack of a control group; limited information regarding dose, duration, and timing of drug exposure; and concomitant use of other medications. These limitations preclude establishing a reliable estimate of the risk of adverse fetal and neonatal outcomes with maternal NSAID use. Because the published safety data on neonatal outcomes involved mostly preterm infants, the generalizability of certain reported risks to the full-term infant exposed to NSAIDs through maternal use is uncertain.

Diclofenac has been shown to cross the placental barrier in humans.

Animal data

Reproductive and developmental studies in animals demonstrated that diclofenac sodium administration during organogenesis did not produce malformations despite the induction of maternal toxicity and fetal toxicity in mice at oral doses up to 20 mg/kg/day (approximately equivalent to the maximum recommended human dose [MRHD] of ZIPSOR, 100 mg/day, based on body surface area (BSA) comparison), and in rats and rabbits at oral doses up to 10 mg/kg/day (approximately 1 and 2 times, respectively, the MRHD based on BSA comparison).

In a study in which pregnant rats were orally administered 2 or 4 mg/kg diclofenac (0.2 and 0.4 times the MRHD based on BSA comparison) from Gestation Day 15 through Lactation Day 21, significant maternal toxicity (peritonitis, mortality) was noted. These maternally toxic doses were associated with dystocia, prolonged gestation, reduced fetal weights and growth, and reduced fetal survival. Diclofenac has been shown to cross the placental barrier in mice and rats.

In published studies, diclofenac administration to pregnant rats prolonged gestation and produced liver toxicity and neuronal loss in offspring (1 mg/kg, IP; 0.1 times the MRHD based on BSA comparison), impaired nephrogenesis in the kidney (3.6 mg/kg, IP; 0.3 times the MRHD based on BSA comparison), and caused adverse effects on the developing testes (6.1 mg/kg, PO; 0.6 times the MRHD based on BSA comparison).

8.2 Lactation

Risk Summary
Data from published literature reports with oral preparations of diclofenac indicate the presence of diclofenac in small amounts human milk (see Data). There are no data on the effects on the breastfed infant, or the effects on milk production. The developmental and health benefits of breastfeeding should be considered along with the mother’s clinical need for ZIPSOR and any potential adverse effects on the breastfed infant from the ZIPSOR or from the underlying maternal condition.

Data
One woman treated orally with a diclofenac salt, 150 mg/day, had a milk diclofenac level of 100 mcg/L, equivalent to an infant dose of about 0.03 mg/kg/day. Diclofenac was not detectable in breast milk in 12 women using diclofenac (after either 100 mg/day orally for 7 days or a single 50 mg intramuscular dose administered in the immediate postpartum period).

8.3 Females and Males of Reproductive Potential

Infertility
Females
Based on the mechanism of action, the use of prostaglandin-mediated NSAIDs, including ZIPSOR, may delay or prevent rupture of ovarian follicles, which has been associated with reversible infertility in some women [see Clinical Pharmacology (12.1)]. Published animal studies have shown that administration of prostaglandin synthesis inhibitors has the potential to disrupt prostaglandin- mediated follicular rupture required for ovulation. Small studies in women treated with NSAIDs have also shown a reversible delay in ovulation. Consider withdrawal of NSAIDs, including ZIPSOR, in women who have difficulties conceiving or who are undergoing investigation of infertility.

Males
Published studies in adult male rodents report that diclofenac, at clinically relevant doses, can produce adverse effects on male reproductive tissues. The impact of these findings on male fertility is not clear [See Nonclinical Toxicology (13.1)].

8.4 Pediatric Use

The safety and effectiveness of ZIPSOR in pediatric patients 12 years to 17 years of age have been established. Use of ZIPSOR in this age group is based on extrapolation of efficacy from adequate and well-controlled studies in adults and supported by pharmacokinetic and safety data from two open-label studies in 49 patients 12 years to 17 years of age with mild to moderate acute pain and one active-controlled study in 76 pediatric patients 12 years to 16 years of age with orthodontic discomfort. Based on the available data, the plasma diclofenac concentration in adolescent patients was comparable to that observed in healthy adults. The safety profile of ZIPSOR in adolescent patients was similar to adults.

The safety and effectiveness of ZIPSOR in patients less than 12 years of age have not been established.

8.5 Geriatric Use

Elderly patients, compared to younger patients, are at greater risk for NSAID-associated serious cardiovascular, gastrointestinal, and/or renal adverse reactions. If the anticipated benefit for the elderly patient outweighs these potential risks, start dosing at the low end of the dosing range, and monitor patients for adverse effects [see Warnings and Precautions (5.1, 5.2, 5.3, 5.6, 5.13)].

Diclofenac is known to be substantially excreted by the kidney, and the risk of adverse reactions to this drug may be greater in patients with impaired renal function. Because elderly patients are more likely to have decreased renal function, care should be taken in dose selection, and it may be useful to monitor renal function.

10 OVERDOSAGE

Symptoms following acute NSAID overdosages have been typically limited to lethargy, drowsiness, nausea, vomiting, and epigastric pain, which have been generally reversible with supportive care. Gastrointestinal bleeding has occurred. Hypertension, acute renal failure, respiratory depression, and coma have occurred, but were rare [see Warnings and Precautions (5.1, 5.2, 5.4, 5.6)].

Manage patients with symptomatic and supportive care following an NSAID overdosage. There are no specific antidotes. Consider emesis and/or activated charcoal (60 to 100 grams in adults, 1 to 2 grams per kg of body weight in pediatric patients) and/or osmotic cathartic in symptomatic patients seen within four hours of ingestion or in patients with a large overdosage (5 to 10 times the recommended dosage). Forced diuresis, alkalinization of urine, hemodialysis, or hemoperfusion may not be useful due to high protein binding.

For additional information about overdosage treatment contact a poison control center (1- 800-222-1222).

11 DESCRIPTION

ZIPSOR (diclofenac potassium) capsule is a nonsteroidal anti-inflammatory drug, available as liquid-filled capsules of 25 mg base, equivalent to 28.3 mg potassium salt for oral administration. Diclofenac potassium is a white to slight yellowish crystalline powder. It is sparingly soluble in water at 25°C. The chemical name is benzeneacetic acid,2-[(2,6- dichlorophenyl) amino]-, monopotassium salt. The molecular weight is 334.24. Its molecular formula is C14H10Cl2NKO2, and it has the following chemical structure.

The inactive ingredients in ZIPSOR include: ProSorb® (a proprietary combination of polyethylene glycol 400, glycerin, sorbitol, povidone, polysorbate 80, and hydrochloric acid), isopropyl alcohol, and mineral oil. The capsule shells contain gelatin, sorbitol, isopropyl alcohol, glycerin, and mineral oil.

12 CLINICAL PHARMACOLOGY

12.1 Mechanism of Action

Diclofenac has analgesic, anti-inflammatory, and antipyretic properties.

The mechanism of action of ZIPSOR, like that of other NSAIDs, is not completely understood but involves inhibition of cyclooxygenase (COX-1 and COX-2).

Diclofenac is a potent inhibitor of prostaglandin synthesis in vitro. Diclofenac concentrations reached during therapy have produced in vivo effects. Prostaglandins sensitize afferent nerves and potentiate the action of bradykinin in inducing pain in animal models. Prostaglandins are mediators of inflammation. Because diclofenac is an inhibitor of prostaglandin synthesis, its mode of action may be due to a decrease of prostaglandins in peripheral tissues.

12.3 Pharmacokinetics

The pharmacokinetics of ZIPSOR was assessed in 24 healthy, normal adult volunteers who received 25 mg ZIPSOR under fasting conditions. The mean pharmacokinetic parameters for ZIPSOR are shown in Table 3. The pharmacokinetics of ZIPSOR was also assessed in pediatric patients 12 to 17 years of age [see Specific Populations: Pediatric] and was found to be similar to adults.

Table 3 Mean Pharmacokinetics of ZIPSOR in Adults
PK Parameter | Number of Subjects | Mean ± Standard Deviation
Tmax (hr) | 24 | 0.47 ± 0.17
Terminal Half-life (hr) | 24 | 1.07 ± 0.29
Cmax (ng/mL) | 24 | 1087 ± 419
AUC(0-∞) (ng·h/mL) | 24 | 597 ± 151

Absorption

Diclofenac is 100% absorbed after oral administration compared to IV administration as measured by urine recovery. However, due to first-pass metabolism, only about 50% of the absorbed dose is systemically available. After repeated oral administration, no accumulation of diclofenac in plasma occurred.

The extent of diclofenac absorption is not significantly affected when ZIPSOR is taken with food. However, the rate of absorption is reduced by food, as indicated by a two-fold increase of Tmax and a 47% decrease in Cmax.

Distribution

The apparent volume of distribution (V/F) of diclofenac potassium is 1.3 L/kg.

Diclofenac is more than 99% bound to human serum proteins, primarily to albumin. Serum protein binding is constant over the concentration range (0.15-105 μg/mL) achieved with recommended doses.

Diclofenac has been shown to cross the placental barrier in humans.

Diclofenac diffuses into and out of the synovial fluid. Diffusion into the joint occurs when plasma levels are higher than those in the synovial fluid, after which the process reverses and synovial fluid levels are higher than plasma levels. It is not known whether diffusion into the joint plays a role in the effectiveness of diclofenac.

Elimination

Metabolism

Five diclofenac metabolites have been identified in human plasma and urine. The metabolites include 4'-hydroxy-, 5-hydroxy-, 3'-hydroxy-, 4',5-dihydroxy- and 3'- hydroxy-4'-methoxy diclofenac. The major diclofenac metabolite, 4'-hydroxy-diclofenac, has very weak pharmacologic activity. The formation of 4'-hydroxy diclofenac is primarily mediated by CPY2C9. Both diclofenac and its oxidative metabolites undergo glucuronidation or sulfation followed by biliary excretion. Acylglucuronidation mediated by UGT2B7 and oxidation mediated by CPY2C8 may also play a role in diclofenac metabolism. CYP3A4 is responsible for the formation of minor metabolites, 5-hydroxy and 3'-hydroxy- diclofenac. In patients with renal dysfunction, peak concentrations of metabolites 4'-hydroxy-and 5-hydroxy-diclofenac were approximately 50% and 4% of the parent compound after single oral dosing compared to 27% and 1% in normal healthy subjects.

Excretion

Diclofenac is eliminated through metabolism and subsequent urinary and biliary excretion of the glucuronide and the sulfate conjugates of the metabolites. Little or no free unchanged diclofenac is excreted in the urine. Approximately 65% of the dose is excreted in the urine, and approximately 35% in the bile as conjugates of unchanged diclofenac plus metabolites. Because renal elimination is not a significant pathway of elimination for unchanged diclofenac, dosing adjustment in patients with mild to moderate renal dysfunction is not necessary. The terminal half-life of unchanged diclofenac is approximately 1 hour.

Specific Populations

Pediatric: The pharmacokinetics of ZIPSOR was assessed in 24 pediatric patients 12 years to 17 years of age with mild to moderate acute pain who received 25 mg ZIPSOR every six hours as needed for pain for up to four days. The mean pharmacokinetic parameters of ZIPSOR on Day 1 in pediatric patients 12 years to 17 years of age are shown in Table 4. Peak plasma levels were noted in one hour, with an elimination half-life of less than 2 hours. The pharmacokinetics of ZIPSOR in pediatric patients 12 years to 17 years of age was similar to that in adults.

Table 4 Mean Pharmacokinetics of ZIPSOR (Day1) in Pediatric Patients 12 Years to 17 Years of Age
PK Parameter | Number of Subjects | Mean ± Standard Deviation
Tmax (hr) | 24 | 0.94 ± 0.42
Terminal Half-life (hr) | 24 | 1.81 ± 0.92
Cmax (ng/mL) | 24 | 699 ± 464
AUC(0-∞) (ng·h/mL) | 24 | 659 ± 208

Race: Pharmacokinetic differences due to race have not been studied.

Hepatic Impairment: Hepatic metabolism accounts for almost 100% of diclofenac elimination. Therefore, in patients with hepatic impairment, start with the lowest dose and if efficacy is not achieved, consider use of an alternate product [see Warnings and Precautions (5.3)].

Renal Impairment: Diclofenac pharmacokinetics has been investigated in subjects with renal insufficiency. In patients with renal impairment (inulin clearance 60-90, 30-60, and <30 mL/min; N=6 in each group), AUC values and elimination rate were comparable to those in healthy subjects [see Warnings and Precautions (5.6)].

Drug Interaction Studies

Aspirin: When NSAIDs were administered with aspirin, the protein binding of NSAIDs were reduced, although the clearance of free NSAID was not altered. The clinical significance of this interaction is not known. See Table 2 for clinically significant drug interactions of NSAIDs with aspirin [see Drug Interactions (7)].

13 NONCLINICAL TOXICOLOGY

13.1 Carcinogenesis, Mutagenesis, Impairment of Fertility

Carcinogenesis

Long-term carcinogenicity studies in rats given diclofenac sodium up to 2 mg/kg/day (approximately 0.2 times the maximum recommended human dose (MRHD) of ZIPSOR, 100 mg/day, based on body surface area (BSA) comparison) have revealed no significant increase in tumor incidence. A 2-year carcinogenicity study conducted in mice employing diclofenac sodium at doses up to 0.3 mg/kg/day (approximately 0.014 times the MRHD based on BSA comparison) in males and 1 mg/kg/day (approximately 0.04 times the MRHD based on BSA comparison) in females did not reveal any oncogenic potential.

Mutagenesis

Diclofenac sodium did not show mutagenic activity in in vitro point mutation assays in mammalian (mouse lymphoma) and microbial (yeast, Ames) test systems and was nonmutagenic in several mammalian in vitro and in vivo tests, including dominant lethal and male germinal epithelial chromosomal aberration studies in Chinese hamsters.

Impairment of Fertility

Diclofenac sodium administered to male and female rats at 4 mg/kg/day (approximately 0.4 times the MRHD based on BSA comparison) did not affect fertility.

However, published studies report that treatment of adult male rats with diclofenac by the oral route at 10 mg/kg (1 times the MRHD based on BSA comparison) for 14 days and at 0.25 mg/kg (0.025 times the MRHD based on BSA comparison) for 30 days produced adverse effects on male reproductive hormones and testes.

14 CLINICAL STUDIES

The efficacy of ZIPSOR in adults was demonstrated in two multicenter, randomized, double-blind, placebo- controlled, parallel arm, multiple-dose clinical trials comparing ZIPSOR 25 mg and placebo in patients with pain following bunionectomy with osteotomy. Once patients met the criteria for randomization (pain intensity ≥4 on a 0-10 numerical pain rating scale) they received their initial dose of study medication followed by a remedication dose when requested by the patient, and were then dosed every six hours over four days. Pain intensity was recorded at 3 and 6 hours postdose during the fixed dosing period. In Study 1, mean baseline pain intensity scores were 6.9 in the ZIPSOR group (range: 4 – 10) and 7.3 in the placebo group (range: 4 – 10). In both studies, patients treated with ZIPSOR had a lower mean pain intensity score over the 48-hour inpatient period following the first remedication dose (see Figure 1). The median time to onset of pain relief was less than one hour for ZIPSOR 25 mg across the clinical trials.

The results were similar in Study 2.

Figure 1 Mean Pain Intensity Scores at the Midpoint and End of Each Dose Interval in Postbunionectomy Pain Study 1

16 HOW SUPPLIED/STORAGE AND HANDLING

ZIPSOR (diclofenac potassium) 25 mg, are translucent, pale yellow, liquid-filled capsules printed with “X592” in black ink supplied as:
Bottles of 120 Capsules NDC# 13913-008-12.

Storage

Store at room temperature 20°C to 25°C (68°F to 77°F); excursions permitted between 15°C to 30°C (59°F to 86°F) [see USP Controlled Room Temperature].

Protect from moisture

Dispense in tight container (USP).

17 PATIENT COUNSELING INFORMATION

Advise the patient to read the FDA-approved patient labeling (Medication Guide) that accompanies each prescription dispensed. Inform patients, families, or their caregivers of the following information before initiating therapy with ZIPSOR and periodically during the course of ongoing therapy.

Cardiovascular Thrombotic Events

Advise patients to be alert for the symptoms of cardiovascular thrombotic events, including chest pain, shortness of breath, weakness, or slurring of speech, and to report any of these symptoms to their health care provider immediately [see Warnings and Precautions (5.1)].

Gastrointestinal Bleeding, Ulceration, and Perforation

Advise patients to report symptoms of ulcerations and bleeding, including epigastric pain, dyspepsia, melena, and hematemesis to their health care provider. In the setting of concomitant use of low-dose aspirin for cardiac prophylaxis, inform patients of the increased risk for and the signs and symptoms of GI bleeding [see Warnings and Precautions (5.2)].

Hepatotoxicity

Inform patients of the warning signs and symptoms of hepatotoxicity (e.g., nausea, fatigue, lethargy, pruritus, diarrhea, jaundice, right upper quadrant tenderness, and “flu-like” symptoms). If these occur, instruct patients to stop ZIPSOR and seek immediate medical therapy [see Warnings and Precautions (5.3)].

Heart Failure and Edema

Advise patients to be alert for the symptoms of congestive heart failure including shortness of breath, unexplained weight gain, or edema and to contact their healthcare provider if such symptoms occur [see Warnings and Precautions (5.5)].

Anaphylactic Reactions

Inform patients of the signs of an anaphylactic reaction (e.g., difficulty breathing, swelling of the face or throat). Instruct patients to seek immediate emergency help if these occur [see Contraindications (4) and Warnings and Precautions (5.7)].

Serious Skin Reactions, including DRESS

Advise patients to stop taking ZIPSOR immediately if they develop any type of rash or fever and to contact their healthcare provider as soon as possible [see Warnings and Precautions (5.9, 5.10)].

Female Fertility

Advise females of reproductive potential who desire pregnancy that NSAIDs, including ZIPSOR, may be associated with a reversible delay in ovulation [see Use in Specific Populations (8.3)].

Fetal Toxicity

Inform pregnant women to avoid use of ZIPSOR and other NSAIDs starting at 30 weeks gestation because of the risk of the premature closing of the fetal ductus arteriosus. If treatment with ZIPSOR is needed for a pregnant woman between about 20 to 30 weeks gestation, advise her that she may need to be monitored for oligohydramnios if treatment continues for longer than 48 hours [see Warnings and Precautions (5.11) and Use in Specific Populations (8.1)].

Avoid Concomitant Use of NSAIDs

Inform patients that the concomitant use of ZIPSOR with other NSAIDs or salicylates (e.g., diflunisal, salsalate) is not recommended due to the increased risk of gastrointestinal toxicity, and little or no increase in efficacy [see Warnings and Precautions (5.2) and Drug Interactions (7)]. Alert patients that NSAIDs may be present in “over the counter” medications for treatment of colds, fever, or insomnia.

Use of NSAIDs and Low-Dose Aspirin

Inform patients not to use low-dose aspirin concomitantly with ZIPSOR until they talk to their healthcare provider [see Drug Interactions (7)].

US Patents: 6,365,180; 7,662,858; 7,884,095; 7,939,518; 8,110,606; 6,287,594; 8,623,920

Distributed by:
Assertio Therapeutics, Inc.
Lake Forest, IL 60045, USA
Issued: 09/2025

Medication Guide for Nonsteroidal Anti-inflammatory Drugs (NSAIDs)

What is the most important information I should know about medicines called Nonsteroidal Anti- inflammatory Drugs (NSAIDs)?

NSAIDs can cause serious side effects, including:

• Increased risk of a heart attack or stroke that can lead to death. This risk may happen early in treatment and may increase:

○ with increasing doses of NSAIDs

○ with longer use of NSAIDs

Do not take NSAIDs right before or after a heart surgery called a “coronary artery bypass graft (CABG)."

Avoid taking NSAIDs after a recent heart attack, unless your healthcare provider tells you to. You may have an increased risk of another heart attack if you take NSAIDs after a recent heart attack.

• Increased risk of bleeding, ulcers, and tears (perforation) of the esophagus (tube leading from the mouth to the stomach), stomach and intestines:

○ anytime during use

○ without warning symptoms

○ that may cause death

The risk of getting an ulcer or bleeding increases with:

○ past history of stomach ulcers, or stomach or intestinal bleeding with use of NSAIDs

○ taking medicines called “corticosteroids”, “anticoagulants”, “SSRIs”, or “SNRIs”

○ increasing doses of NSAIDs

○ longer use of NSAIDs

○ smoking

○ drinking alcohol

○ older age

○ poor health

○ advanced liver disease

○ bleeding problems

NSAIDs should only be used:

○ exactly as prescribed

○ at the lowest dose possible for your treatment

○ for the shortest time needed

What are NSAIDs?

NSAIDs are used to treat pain and redness, swelling, and heat (inflammation) from medical conditions such as different types of arthritis, menstrual cramps, and other types of short-term pain.

Who should not take NSAIDs?

Do not take NSAIDs:

- if you have had an asthma attack, hives, or other allergic reaction with aspirin or any other NSAIDs.
- right before or after heart bypass surgery.

Before taking NSAIDS, tell your healthcare provider about all of your medical conditions, including if you:

- have liver or kidney problems
- have high blood pressure
- have asthma
- are pregnant or plan to become pregnant. Taking NSAIDs at about 20 weeks of pregnancy or later may harm your unborn baby. If you need to take NSAIDs for more than 2 days when you are between 20 and 30 weeks of pregnancy, your healthcare provider may need to monitor the amount of fluid in your womb around your baby. You should not take NSAIDs after about 30 weeks of pregnancy.
- are breastfeeding or plan to breast feed.

Tell your healthcare provider about all of the medicines you take, including prescription or over-the- counter medicines, vitamins or herbal supplements. NSAIDs and some other medicines can interact with each other and cause serious side effects. Do not start taking any new medicine without talking to your healthcare provider first.

What are the possible side effects of NSAIDs?

NSAIDs can cause serious side effects, including:

See “What is the most important information I should know about medicines called Nonsteroidal Anti- inflammatory Drugs (NSAIDs)?

- new or worse high blood pressure
- heart failure
- liver problems including liver failure
- kidney problems including kidney failure
- low red blood cells (anemia)
- life-threatening skin reactions
- life-threatening allergic reactions
- Other side effects of NSAIDs include: stomach pain, constipation, diarrhea, gas, heartburn, nausea, vomiting, and dizziness.

Get emergency help right away if you get any of the following symptoms:

- shortness of breath or trouble breathing
- chest pain
- weakness in one part or side of your body
- slurred speech
- swelling of the face or throat

Stop taking your NSAID and call your healthcare provider right away if you get any of the following symptoms:

- nausea
- more tired or weaker than usual
- diarrhea
- itching
- your skin or eyes look yellow
- indigestion or stomach pain
- flu-like symptoms
- vomit blood
- there is blood in your bowel movement or it is black and sticky like tar
- unusual weight gain
- skin rash or blisters with fever
- swelling of the arms, legs, hands and feet

If you take too much of your NSAID, call your healthcare provider or get medical help right away.

These are not all the possible side effects of NSAIDs. For more information, ask your healthcare provider or pharmacist about NSAIDs.

Call your doctor for medical advice about side effects. You may report side effects to FDA at 1-800-FDA-1088.

Other information about NSAIDs

- Aspirin is an NSAID but it does not increase the chance of a heart attack. Aspirin can cause bleeding in the brain, stomach, and intestines. Aspirin can also cause ulcers in the stomach and intestines.
- Some NSAIDs are sold in lower doses without a prescription (over-the counter). Talk to your healthcare provider before using over-the-counter NSAIDs for more than 10 days.

General information about the safe and effective use of NSAIDs

Medicines are sometimes prescribed for purposes other than those listed in a Medication Guide. Do not use NSAIDs for a condition for which it was not prescribed. Do not give NSAIDs to other people, even if they have the same symptoms that you have. It may harm them.

If you would like more information about NSAIDs, talk with your healthcare provider. You can ask your pharmacist or healthcare provider for information about NSAIDs that is written for health professionals.

Distributed by: Assertio Therapeutics, Inc., Lake Forest, IL 60045
For more information, go to www.ZIPSOR.com or call 1-866-458-6389

This Medication Guide has been approved by the U.S. Food and Drug Administration.

Issued or Revised: April 2021 ZIP-001-C.7

Principal Display Panel - 25 mg - 120-count Bottle Label

NDC 13913-008-12

Rx Only

ZIPSOR®
(diclofenac potassium)

120 Liquid Filled Capsules